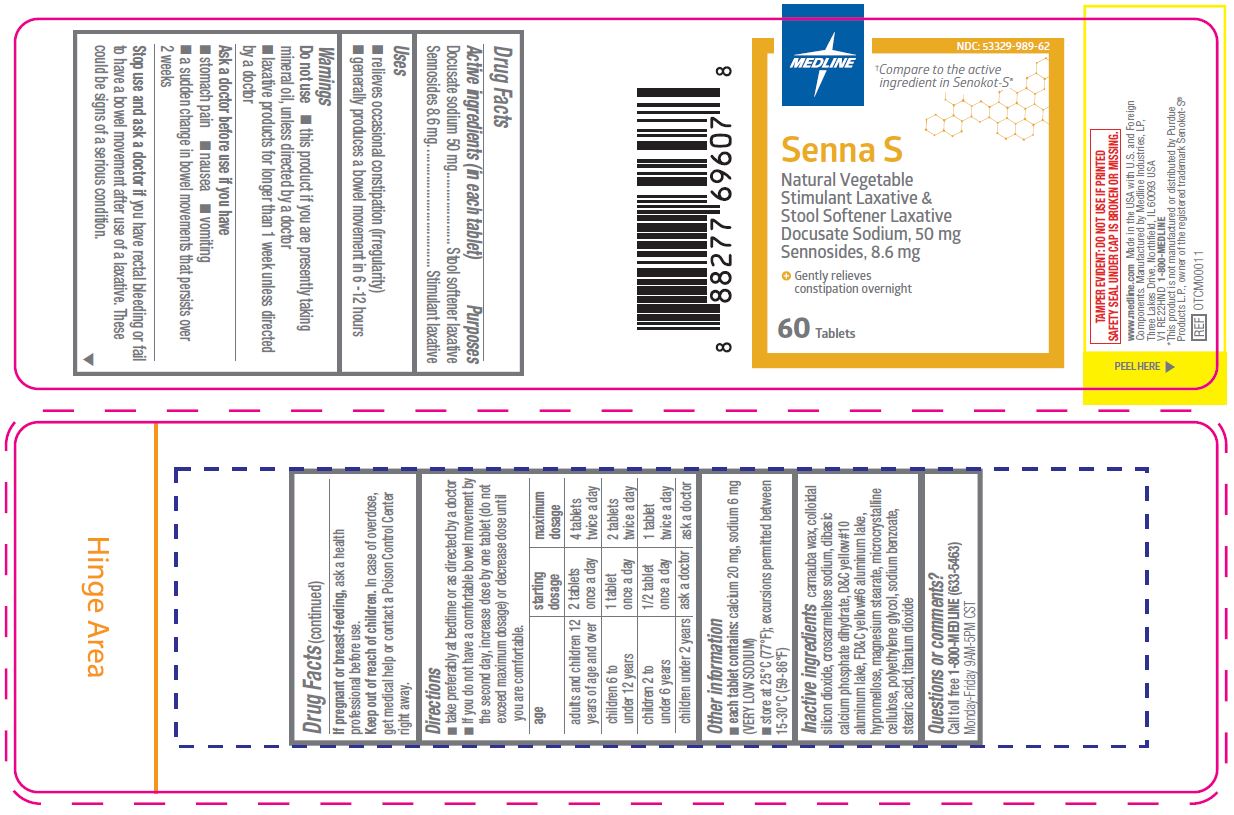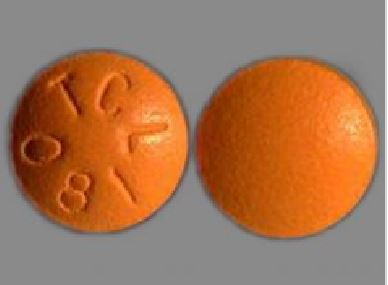 DRUG LABEL: Senna S
NDC: 53329-989 | Form: TABLET, COATED
Manufacturer: Medline Industries, LP
Category: otc | Type: HUMAN OTC DRUG LABEL
Date: 20241126

ACTIVE INGREDIENTS: DOCUSATE SODIUM 50 mg/1 1; SENNOSIDES 8.6 mg/1 1
INACTIVE INGREDIENTS: TITANIUM DIOXIDE; CARNAUBA WAX; SILICON DIOXIDE; CALCIUM PHOSPHATE, DIBASIC, DIHYDRATE; FD&C YELLOW NO. 6; CROSCARMELLOSE SODIUM; D&C YELLOW NO. 10; HYPROMELLOSE, UNSPECIFIED; MAGNESIUM STEARATE; MICROCRYSTALLINE CELLULOSE; POLYETHYLENE GLYCOL, UNSPECIFIED; SODIUM BENZOATE; STEARIC ACID

989 Senna S Sennosides 8.6mg and Docusate Sodium 50mg

Active ingredient (in each tablet)

- Docusate sodium 50 mg
- Sennosides 8.6 mg

Purpose

Stool softener laxative

Stimulant laxative

Uses

- relieves occasional constipation (irregularity)
- generally produces a bowel movement in 6 -12 hours

Warnings

Do not use

- this product if you are presently taking mineral oil, unless directed by a doctor
- laxative products for longer than 1 week unless directed by a doctor

Ask a doctor before use if you have

- stomach pain
- nausea
- vomiting
- a sudden change in bowel movements that persists over 2 weeks

Stop use and ask a doctor if

you have rectal bleeding or fail to have a bowel movement after use of a laxative. These could be signs of a serious condition.

If pregnant or breast-feeding,

ask a health professional before use.

Keep out of reach of children.

In case of overdose, get medical help or contact a Poison Control Center right away.

Directions

- take preferably at bedtime or as directed by a doctor
- if you do not have a comfortable bowel movement by the second day, increase dose by one tablet (do not exceed maximum dosage) or decrease dose until you are comfortable

age | starting; dosage | maximum; dosage
adults and children 12; years of age and over | 2 tablets; once a day | 4 tablets; twice a day
children 6 to; under 12 years | 1 tablet; once a day | 2 tablets; twice a day
children 2 to; under 6 years | 1/2 tablet; once a day | 1 tablet; twice a day
children under 2 years | ask a doctor | ask a doctor

Other information

- each tablet contains: calcium 20 mg, sodium 6 mg (VERY LOW SODIUM)
- store at 25°C (77°F); excursions permitted between 15-30°C (59-86°F)

Inactive ingredients

carnauba wax, colloidal silicon dioxide, croscarmellose sodium, dibasic calcium phosphate dihydrate, D&C yellow#10 aluminum lake, FD&C yellow#6 aluminum lake, hypromellose, magnesium stearate, microcrystalline cellulose, polyethylene glycol, sodium benzoate, stearic acid, titanium dioxide

Questions or comments?

Call toll free 1-800-MEDLINE (633-5463)
Monday-Friday 9AM-5PM CST

Manufacturing Information

Manufactured for:
Medline Industries, LP
Three Lakes Drive, Northfield, IL 60093 USA
Made in USA with domestic and foreign materials
www.medline.com
1-800-MEDLINE (633-5463)
REF: OTCM00011
V1 RE22HND